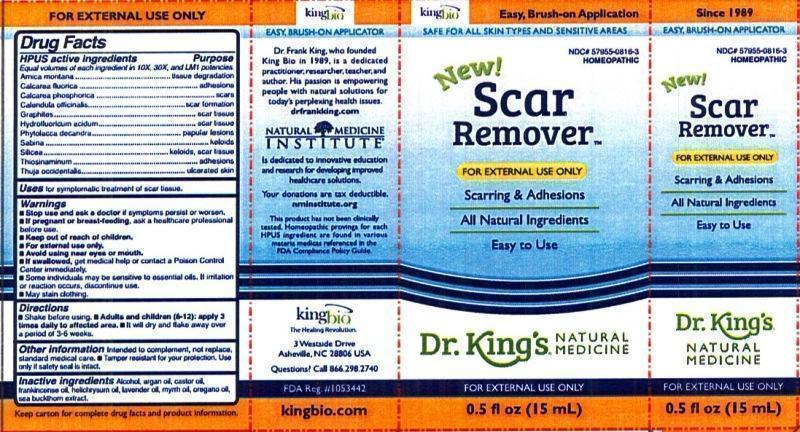 DRUG LABEL: Scar Remover
NDC: 57955-0816 | Form: LIQUID
Manufacturer: King Bio Inc.
Category: homeopathic | Type: HUMAN OTC DRUG LABEL
Date: 20151021

ACTIVE INGREDIENTS: ARNICA MONTANA 10 [hp_X]/15 mL; CALCIUM FLUORIDE 10 [hp_X]/15 mL; TRIBASIC CALCIUM PHOSPHATE 10 [hp_X]/15 mL; CALENDULA OFFICINALIS FLOWERING TOP 10 [hp_X]/15 mL; GRAPHITE 10 [hp_X]/15 mL; HYDROFLUORIC ACID 10 [hp_X]/15 mL; PHYTOLACCA AMERICANA ROOT 10 [hp_X]/15 mL; JUNIPERUS SABINA LEAFY TWIG 10 [hp_X]/15 mL; SILICON DIOXIDE 10 [hp_X]/15 mL; ALLYLTHIOUREA 10 [hp_X]/15 mL; THUJA OCCIDENTALIS LEAFY TWIG 10 [hp_X]/15 mL
INACTIVE INGREDIENTS: ALCOHOL; ARGAN OIL; CASTOR OIL; FRANKINCENSE OIL; HELICHRYSUM ITALICUM FLOWER OIL; LAVENDER OIL; MYRRH OIL; OREGANO LEAF OIL; HIPPOPHAE RHAMNOIDES FRUIT OIL

Scar Remover™

Drug Facts

___________________________________________________________________________________________________________________

HPUS active ingredients: Arnica montana, Calcarea fluorica, Calcarea phosphorica, Calendula officinalis, Graphites, Hydrofluoricum acidum, Phytolacca decandra, Sabina, Silicea, Thiosinaminum, Thuja occidentalis. Equal volumes of each ingredient in 10X, 30X, and LM1 potencies.

INDICATIONS AND USAGE

Uses for symptomatic treatment of scar tissue.

Warnings

- Stop use and ask your doctor if symptoms persist or worsen.
- If pregnant or breast-feeding, ask a healthcare professional before use.
- Keep out of reach of children.
- For external use only.
- Avoid using near eyes or mouth.
- If swallowed, get medical help or contact a Poison Control Center immediately.
- Some individuals may be sensitive to essential oils. If irritation or reaction occurs, discontinue use.
- May stain clothing.

- Keep out of reach of children.

DOSAGE AND ADMINISTRATION

Directions • Shake before using. • Adults and children (6-12): apply 3 times daily to affected area. • It will dry and flake away over a period of 3-6 weeks.

Other information:Intended to complement, not replace, standard medical care. Tamper resistant for your protection. Use only if safety seal is intact.

INACTIVE INGREDIENT

Inactive ingredients: Alcohol, argan oil, castor oil, frankincense oil, helichrysum oil, lavender oil, myrrh oil, oregano oil, sea buckthorn extract.

Drug Facts

___________________________________________________________________________________________________________________

HPUS active ingredients Purpose

Equal volumes of each ingredient in 10X, 30X, and LM1 potencies.

Arnica montana......................................................tissue degradation

Calcarea fluorica.....................................................adhesions

Calcarea phosphorica...............................................scars

Calendula officinalis.................................................scar formation

Graphites...............................................................scar tissue

Hydrofluoricum acidum............................................scar tissue

Phytolacca decandra................................................papular lesions

Sabina...................................................................keloids

Silicea....................................................................keloids, scar tissue

Thiosinaminum........................................................adhesions

Thuja occidentalis....................................................ulcerated skin